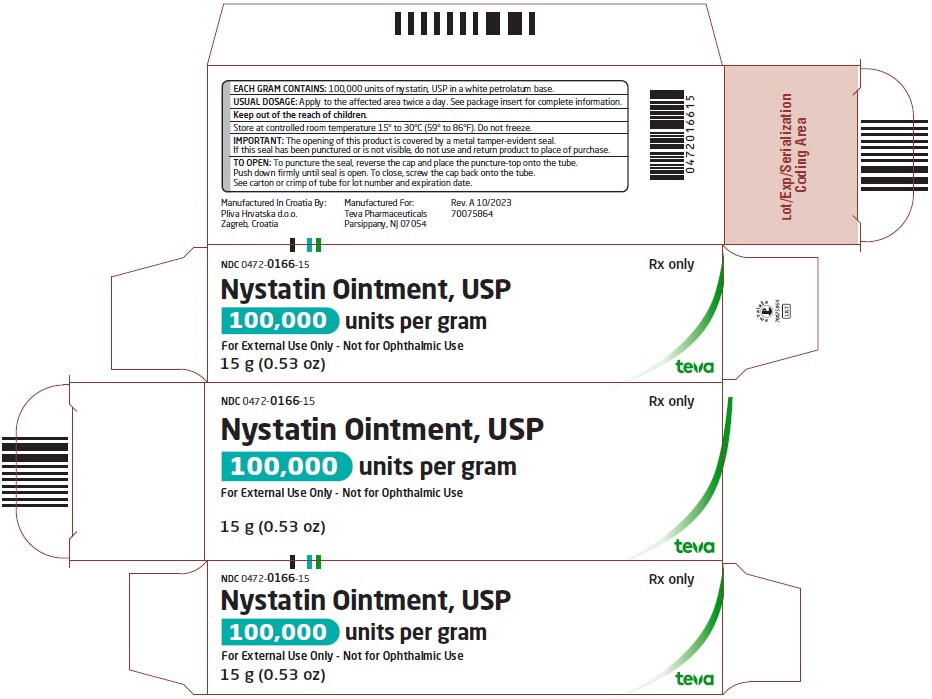 DRUG LABEL: Nystatin
NDC: 0472-0166 | Form: OINTMENT
Manufacturer: Actavis Pharma, Inc.
Category: prescription | Type: HUMAN PRESCRIPTION DRUG LABEL
Date: 20231030

ACTIVE INGREDIENTS: NYSTATIN 100000 [USP'U]/1 g
INACTIVE INGREDIENTS: PETROLATUM

NYSTATIN OINTMENT, USP
(100,000 units/g)

Rx only

DESCRIPTION

Each gram of nystatin ointment, USP contains 100,000 units of nystatin in a white petrolatum base.

CLINICAL PHARMACOLOGY

Nystatin is an antifungal antibiotic which is both fungistatic and fungicidal in vitro, against a wide variety of yeasts and yeast-like fungi. It probably acts by binding to sterols in the cell membrane of the fungus with a resultant change in membrane permeability allowing leakage of intracellular components. Nystatin is a polyene antibiotic of undetermined structural formula that is obtained from Streptomyces noursei, and is the first well tolerated antifungal antibiotic of dependable efficacy for the treatment of cutaneous, oral and intestinal infections caused by Candida (Monilia) albicans and other Candida species. It exhibits no appreciable activity against bacteria.

Nystatin provides specific therapy for all localized forms of candidiasis. Symptomatic relief is rapid, often occurring within 24 to 72 hours after the initiation of treatment. Cure is effected both clinically and mycologically in most cases of localized candidiasis.

INDICATIONS AND USAGE

Nystatin ointment, USP is indicated in the treatment of cutaneous or mucocutaneous mycotic infections caused by Candida (Monilia) albicans and other Candida species.

CONTRAINDICATIONS

Nystatin ointment, USP is contraindicated in patients with a history of hypersensitivity to any of its components.

PRECAUTIONS

Should a reaction of hypersensitivity occur the drug should be immediately withdrawn and appropriate measures taken.

ADVERSE REACTIONS

Nystatin is virtually nontoxic and nonsensitizing and is well tolerated by all age groups including debilitated infants, even on prolonged administration.

If irritation on topical application should occur, discontinue medication.

DOSAGE AND ADMINISTRATION

Nystatin ointment, USP should be applied liberally to the affected areas twice a day or as indicated until healing is complete. The ointment does not stain the skin or mucous membranes and it provides a simple, convenient means of treatment.

HOW SUPPLIED

Nystatin ointment, USP 100,000 units/g is available as follows:

15 g tube (0.53 oz) NDC 0472-0166-15

30 g tube (1.1 oz) NDC 0472-0166-30

Store at controlled room temperature 15° to 30°C (59° to 86°F). Do not freeze.

Manufactured In Croatia By:

Pliva Hrvatska d.o.o.

Zagreb, Croatia

Manufactured For:

Teva Pharmaceuticals

Parsippany, NJ 07054

Rev. A 10/2023

PACKAGE LABEL.PRINCIPAL DISPLAY PANEL

NDC 0472-0166-15

Nystatin Ointment, USP

100,000 units per gram

Rx only

For External Use Only - Not for Ophthalmic Use

15 g (0.53 oz)